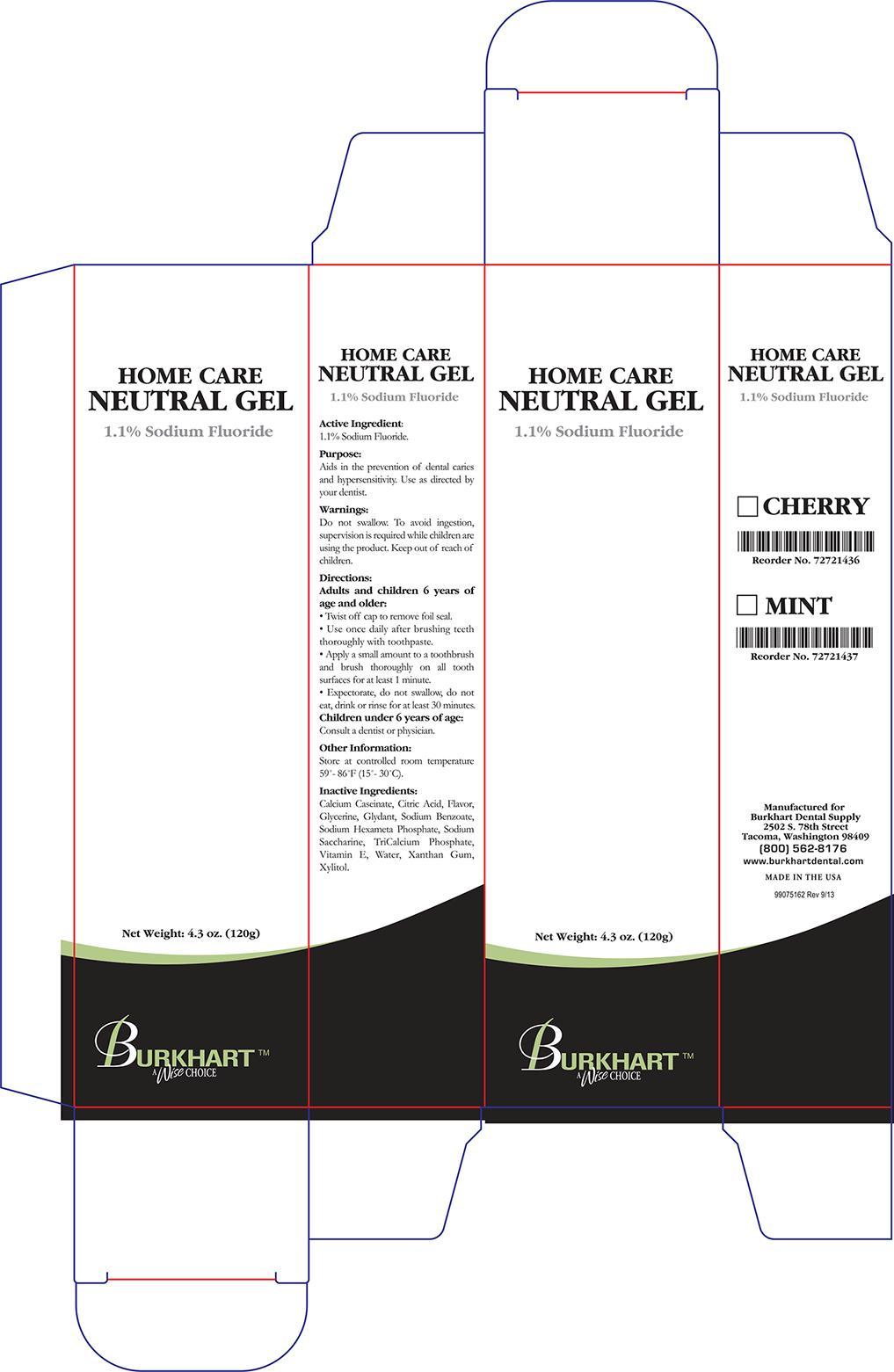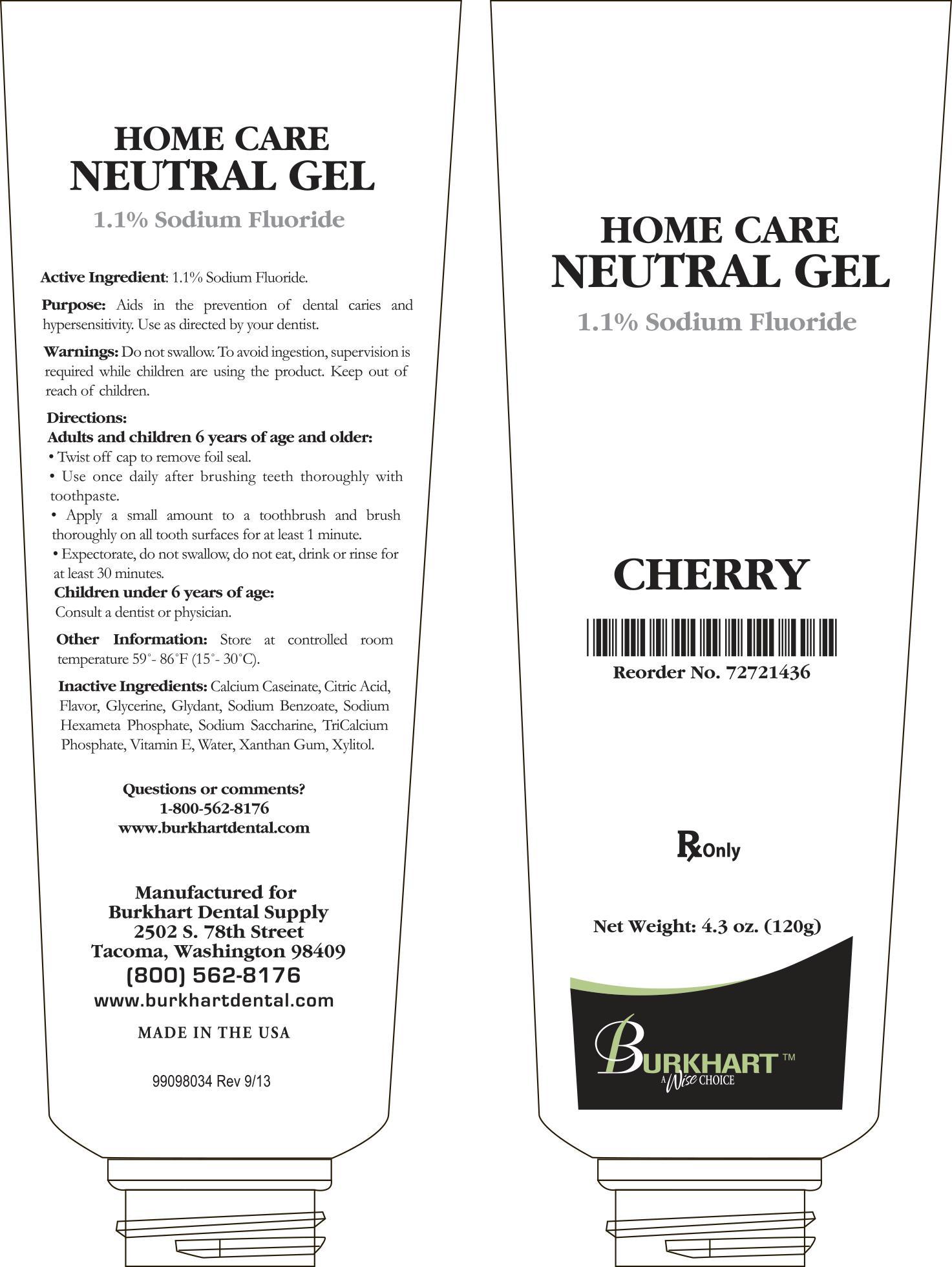 DRUG LABEL: Burkhart Neutral
NDC: 43498-301 | Form: GEL
Manufacturer: Burkhart Dental Supply Inc
Category: prescription | Type: HUMAN PRESCRIPTION DRUG LABEL
Date: 20190211

ACTIVE INGREDIENTS: SODIUM FLUORIDE 0.597 g/120 g
INACTIVE INGREDIENTS: CASEIN; CITRIC ACID MONOHYDRATE; GLYCERIN; DMDM HYDANTOIN; SODIUM BENZOATE; SODIUM POLYMETAPHOSPHATE; SACCHARIN SODIUM; TRICALCIUM PHOSPHATE; .ALPHA.-TOCOPHEROL; WATER; XANTHAN GUM; XYLITOL

Active Ingredient:

1.1% Sodium Fluoride.

Purpose:

Aids in prevention of dental caries and hypersensitivity. Use as directed by your dentist.

Warnings:

Do not swallow. To avoid ingestion, supervision is required while children are using the product. Keep out of reach of children.

Directions:

Adults and children 6 years of age and older:

- Twist off cap to remove foil seal.
- Use once daily after brushing teeth thoroughly with toothpaste.
- Apply a small amount to a toothbrush and brush thoroughly on all tooth surfaces for at least 1 minute.
- Expectorate, do not swallow, do not eat, drink or rinse for at least 30 minutes.

Children under 6 years of age:

- Consult a dentist or physcian.

STORAGE AND HANDLING

Store at controlled room temperature 59° - 86°F (15° - 30°C).

Inactive Ingredients:

Calcium Caseinate, Citric Acid, Flavor, Glycerine, Glydant, Sodium Benzoate, Sodium Hexameta Phosphate, Sodium Saccharine, TriCalcium Phosphate, Vitamin E, Water, Xanthan Gum, Xylitol.